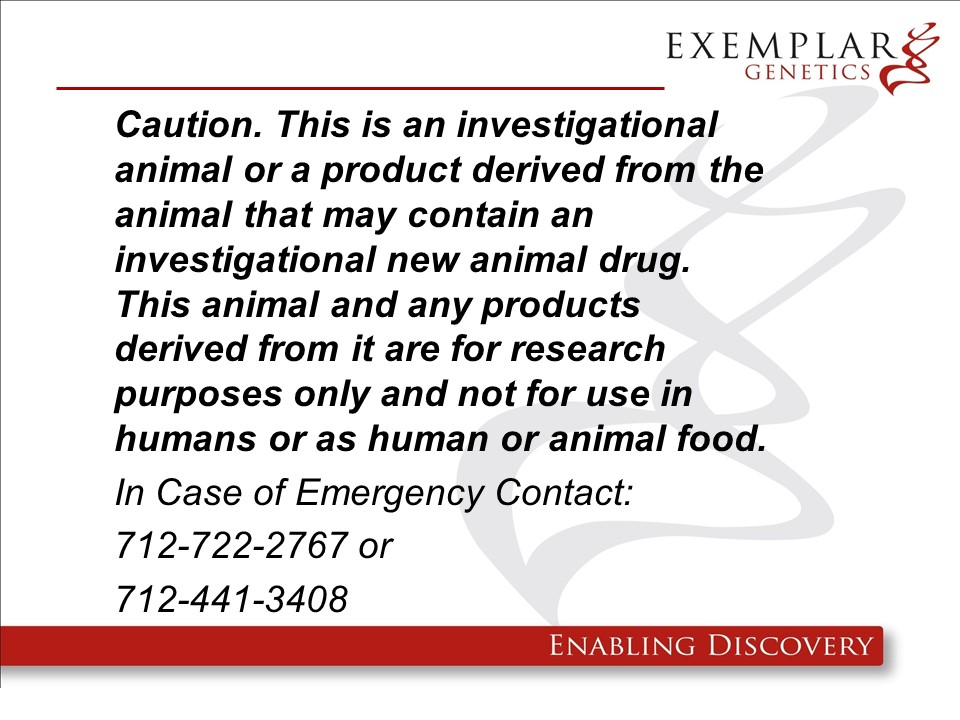 DRUG LABEL: ExeGen SCN5A Miniswine
NDC: 86093-1902 | Form: NOT APPLICABLE
Manufacturer: Exemplar Genetics Llc
Category: other | Type: INTENTIONAL ANIMAL GENOMIC ALTERATION LABEL
Date: 20250630

ACTIVE INGREDIENTS: SCN5A-NEO Construct at Exon 11 in Yucatan Minipig (SCNA +/-) 1 [arb'U]/1 [arb'U]

SCN5A-NEO Construct at Exon 11 in Yucatan Minipig (SCNA +/-)

ExeGen SCN5A miniswine are geneticaly engineered yucatan miniature swine containing the rDNA construct pSCN5A-Neo which exibit similar phenotypes to human patients with sudden arrhythmia death syndromes (SADS). These pigs are intended to be used as large animal models of the human disease. We will not be requesting a food use authorizaiton and the carcasses and all materials generated from these animals will be destroyed by incineration.

Product Definition: A specific line of Yucatan miniature pigs (Sus scrofa domesticus), including heterozygous offspring resulting from a heterozygous founder in which the SCN5A gene has been disrupted by the homologous recombinaiton of a single copy of a pSCN5A-Neo construct in exon 11, for use in biomedical research.

Warning: This product is from a genetically engineered animal and may contain an investigational new animal drug. It is for research purposes only and not for use in humans or as food/feed unless authorization has been granted by the US Food and Drug Administration. In case of emergency or release contact Exemplar Genetics at 712-722-2767 or 712-441-3408.